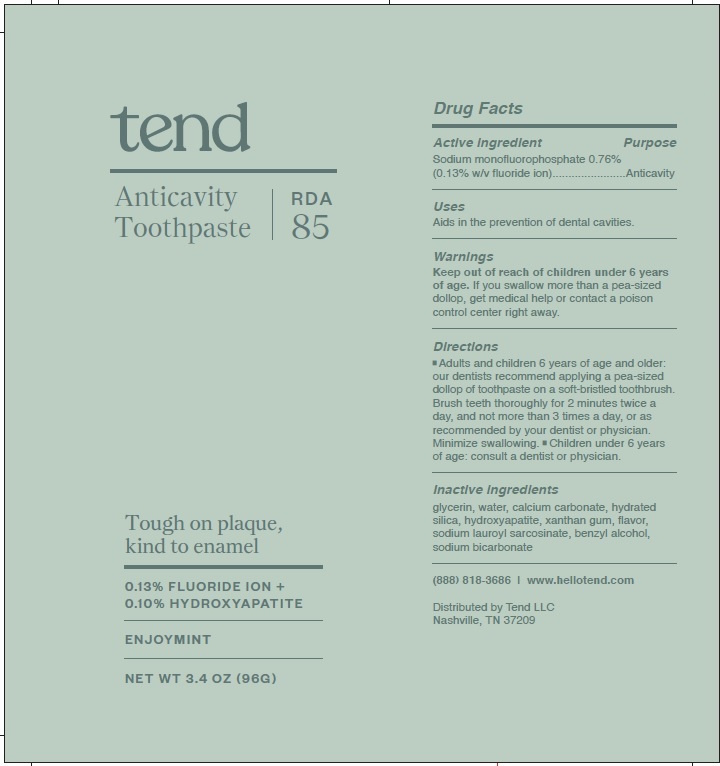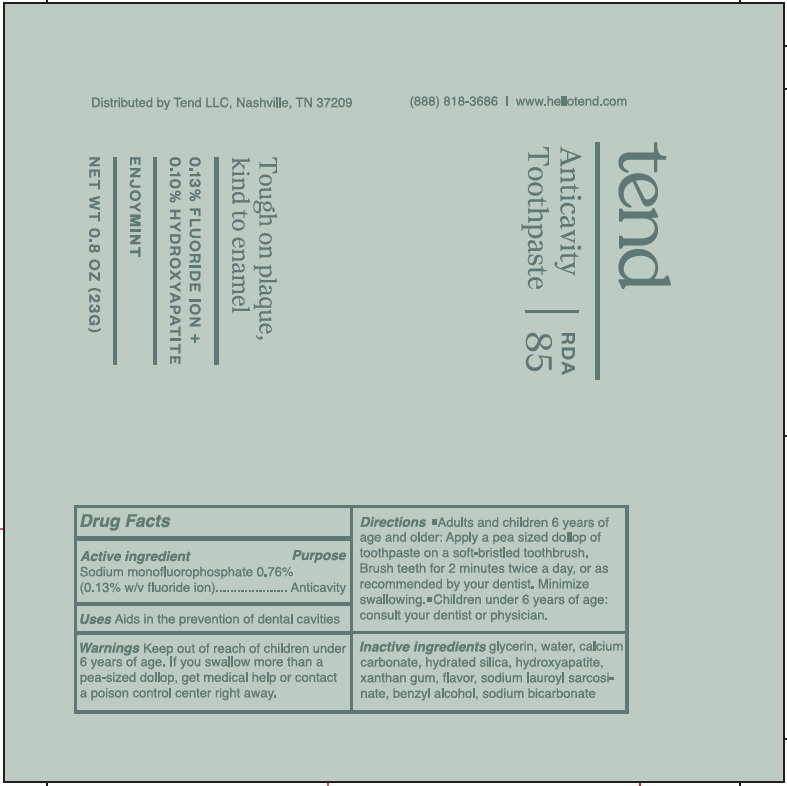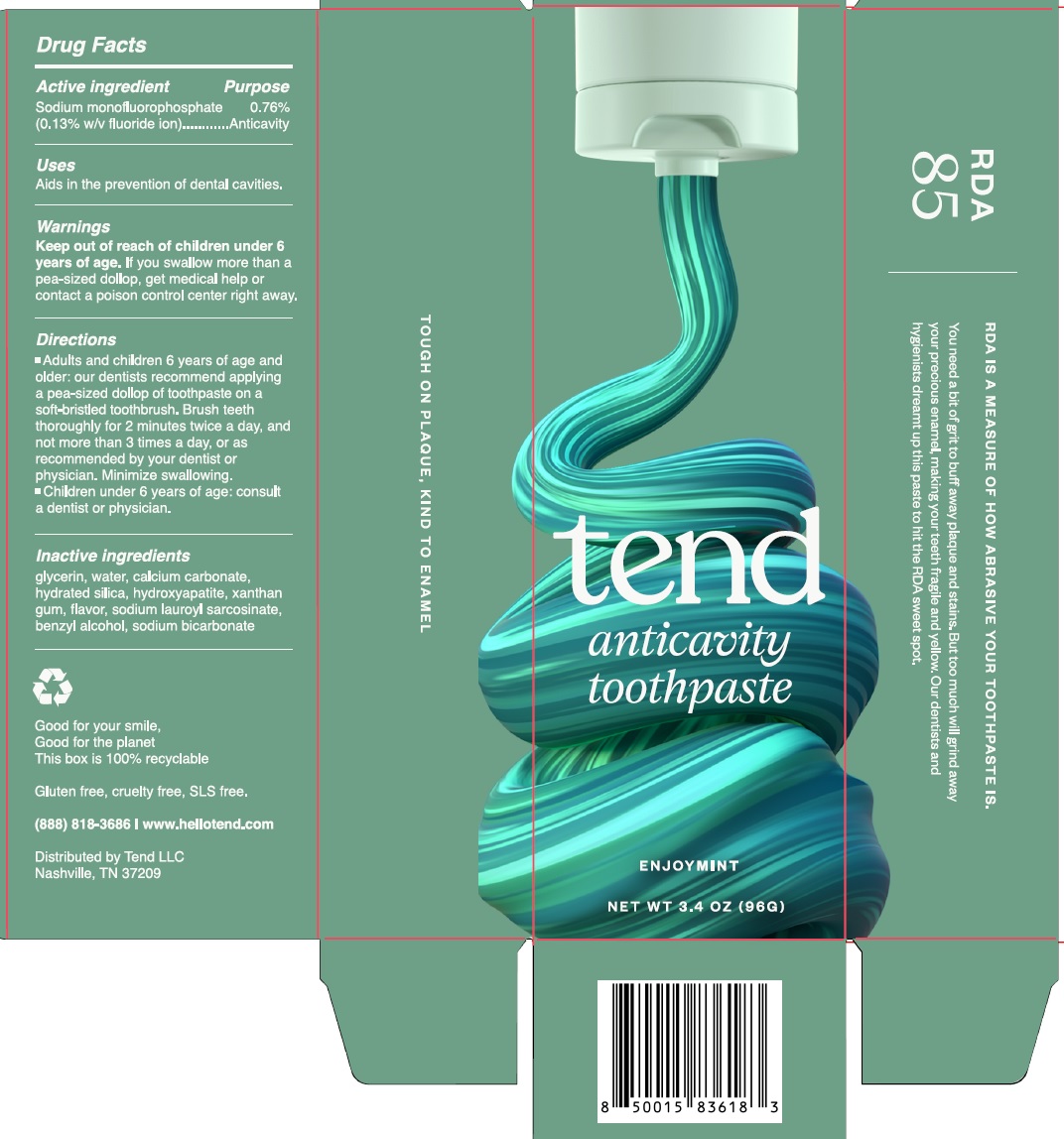 DRUG LABEL: Tend Anticavity
NDC: 78594-000 | Form: GEL
Manufacturer: Tend, LLC
Category: otc | Type: HUMAN OTC DRUG LABEL
Date: 20230622

ACTIVE INGREDIENTS: SODIUM MONOFLUOROPHOSPHATE 1.3 mg/1 g
INACTIVE INGREDIENTS: GLYCERIN; WATER; CALCIUM CARBONATE; HYDRATED SILICA; TRIBASIC CALCIUM PHOSPHATE; XANTHAN GUM; SODIUM LAUROYL SARCOSINATE; BENZYL ALCOHOL; SODIUM BICARBONATE

Tend Enjoymint Anticavity toothpaste

Active ingredient

Sodium monofluorophosphate 0.76% (0.13% w/v fluoride ion)

Purpose

Anticavity

Uses

Aids in the prevention of dental cavities.

Warnings

Keep out of reach of children

under 6 years of age.If you swallow more than a pea-sized dollop, get medical help or contact a poison control center right away.

Directions

- Adults and children 6 years of age and older: our dentists recommend applying a pea-sized dollop of toothpaste on a soft-bristled toothbrush. Brush teeth thoroughly for 2 minutes twice a day, and not more than 3 times a day, or as recommended by your dentist or hysician. Minimize swallowing.
- Children under 6 years of age: consult a dentist or physician.

Inactive ingredients

glycerin, water, calcium carbonate, hydrated silica, hydroxyapatite, xanthan gum, flavor, sodium lauroyl sarcosinate, benzyl alcohol, sodium bicarbonate

QUESTIONS

(888) 818-3686 www.hellotend.com